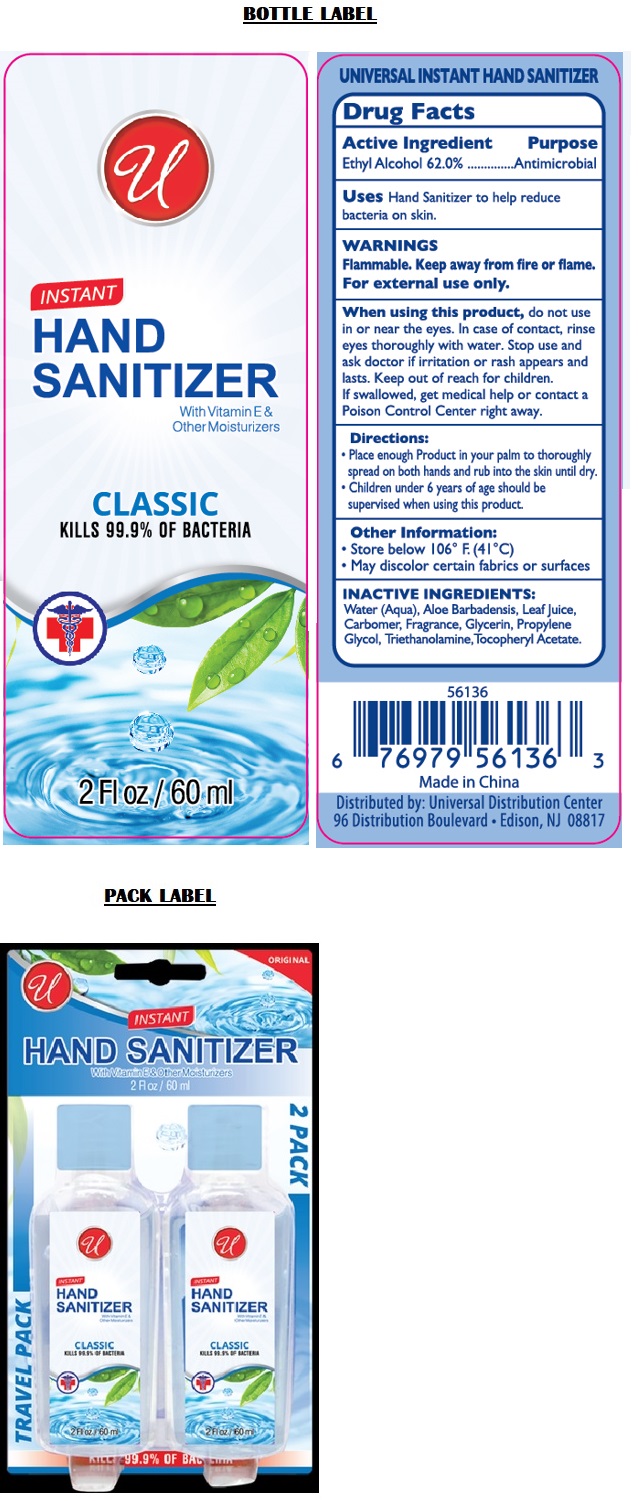 DRUG LABEL: 2PK TRAVELER HAND SANITIZER CLASSIC
NDC: 52000-116 | Form: GEL
Manufacturer: Universal Distribution Center LLC
Category: otc | Type: HUMAN OTC DRUG LABEL
Date: 20211125

ACTIVE INGREDIENTS: ALCOHOL 0.62 mL/1 mL
INACTIVE INGREDIENTS: WATER; ALOE VERA LEAF; CARBOMER HOMOPOLYMER, UNSPECIFIED TYPE; GLYCERIN; PROPYLENE GLYCOL; TROLAMINE; .ALPHA.-TOCOPHEROL ACETATE

TRAVEL PACK INSTANT HAND SANITIZER CLASSIC

Active Ingredient

Ethyl Alcohol 62.0%

Purpose

Antimicrobial

Uses

Hand Sanitizer to help reduce bacteria on skin.

WARNINGS

Flammable. Keep away from fire or flame.

For external use only.

When using this product, do not use in or near the eyes. In case of contact, rinse eyes thoroughly with water. Stop use and ask doctor if irritation or rash appears and lasts.

KEEP OUT OF REACH OF CHILDREN

Keep out of reach for children. If swallowed, get medical help or contact a Poison Control Center right away.

Directions:

• Place enough Product in your palm to thoroughly spread on both hands and rub into the skin until dry.
• Children under 6 years of age should be supervised when using this product.

Other Information:

• Store below 106° F (41°C)
• May discolor certain fabrics or surfaces

INACTIVE INGREDIENTS:

Water(Aqua), Aloe Barbadensis Leaf Juice, Carbomer, Fragrance, Glycerin, Propylene Glycol, Triethanolamine, Tocopheryl Acetate.

With Vitamin E & Other Moisturizers

KILLS 99.9% OF BACTERIA

UNIVERSAL INSTANT HAND SANITIZER

Made in China

Distributed by: Universal Distribution Center
96 Distribution Boulevard • Edison, NJ 08817